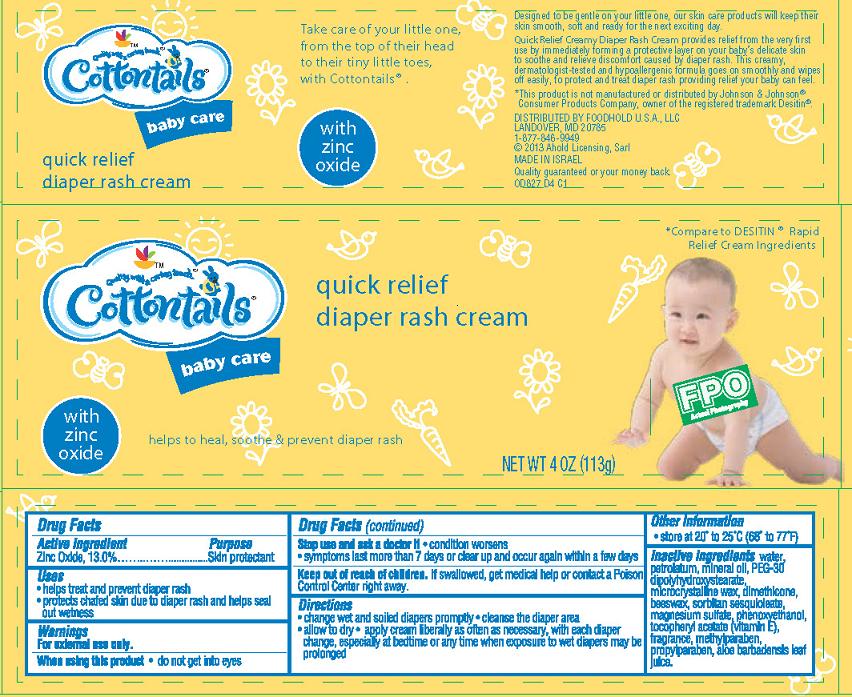 DRUG LABEL: Quick Relief Creamy Diaper Rash
NDC: 41520-827 | Form: CREAM
Manufacturer: American Sales Company
Category: otc | Type: HUMAN OTC DRUG LABEL
Date: 20130930

ACTIVE INGREDIENTS: ZINC OXIDE 130 mg/1 g
INACTIVE INGREDIENTS: WATER; PETROLATUM; MINERAL OIL; PEG-30 DIPOLYHYDROXYSTEARATE; MICROCRYSTALLINE WAX; DIMETHICONE; YELLOW WAX; SORBITAN SESQUIOLEATE; MAGNESIUM SULFATE; PHENOXYETHANOL; .ALPHA.-TOCOPHEROL ACETATE; METHYLPARABEN; PROPYLPARABEN; ALOE VERA LEAF

Cottontails Quick Relief Creamy Diaper Rash Cream

Active ingredient

Zinc Oxide........13.0%

Purpose

Skin Protectant

Uses

- helps treat and prevent diaper rash
- protects chafed skin due to diaper rash and helps seal out wetness

Warnings

For external use only.

When using this product

- do not get into eyes

Stop use and ask a doctor if

- condition worsens
- symptoms last more than 7 days or clear up and occur again within a few days

Keep Out of Reach of Children.

If swallowed, get medical help or contact a Poison Control Center right away.

Directions

- change wet and soiled diapers promptly
- cleanse the diaper area
- allow to dry
- apply cream liberally as often as necessary, with each diaper change, especially at bedtime or any time when exposure to wet diapers may be prolonged

Other Information

- store at 20º to 25ºC (68º to 77ºF)

Inactive ingredients

water, petrolatum, mineral oil, PEG-30 dipolyhydroxystearate, microcrystalline wax, dimethicone, beeswax, sorbitan sesquioleate, magnesium sulfate, phenoxyethanol, tocopheryl acetate (Vitamin E), fragrance, methylparaben, propylparaben, aloe barbadensis leaf juice

Package/Label Principal Display Panel

Cottontails baby care quick relief diaper rash cream

Take care of your little one, from the top of their head to their tiny little toes, with Cottontails®.

With zinc oxide

Helps to heal, soothe & prevent diaper rash

Compare to Desitin® Rapid Relief Cream Ingredients

NET WT. 4 OZ. (113 g)

Designed to be gentle on your little one, our skin care products will keep their skin smooth, soft and ready for the next exciting day.

Quick Relief Creamy Diaper Rash Cream provides relief from the very first use by immediately forming a protective layer on your baby's delicate skin to soothe and relieve discomfort caused by diaper rash. This creamy, dermatologist-tested and hypoallergenic formula goes on smoothly and wipes off easily, to protect and treat diaper rash providing relief your baby can feel.

*This product is not manufactured or distributed by Johnson & Johnson® Consumer Products Company, owner of the registered trademark Desitin®

DISTRIBUTED BY FOODHOLD U.S.A., LLC
LANDOVER, MD 20785
1-877-846-9949
© 2013 Ahold Licensing, Sarl

MADE IN INSRAEL
Quality guaranteed or your money back.
0D827 D4 C1

Carton Label